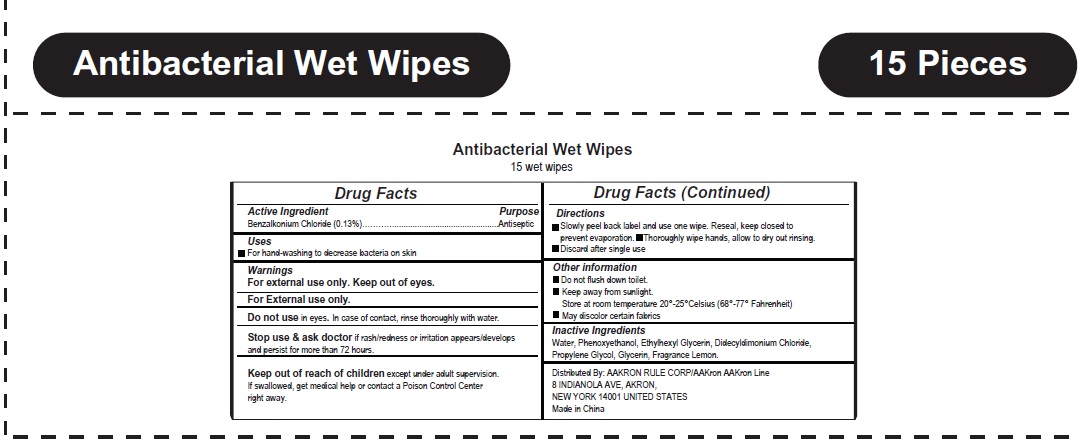 DRUG LABEL: Antibacterial Wet Wipes
NDC: 69394-005 | Form: CLOTH
Manufacturer: AAkron Rule Corporation
Category: otc | Type: HUMAN OTC DRUG LABEL
Date: 20230822

ACTIVE INGREDIENTS: BENZALKONIUM CHLORIDE 0.13 g/100 mL
INACTIVE INGREDIENTS: ETHYLHEXYLGLYCERIN; PHENOXYETHANOL; WATER; PROPYLENE GLYCOL; DIDECYLDIMONIUM CHLORIDE; FRAGRANCE LEMON ORC2001060; GLYCERIN

Active Ingredient

Benzalkonium Chloride (0.13%)

Purpose

Antiseptic

Use

For hand-washing to decrease bacteria on skin

Warnings

- Flammable. Keep away from heat and flame.
- For External use only.
- Do not usein eyes. In case of contact, rinse thoroughly with water.
- Stop use & ask doctorif rash/redness or irritation appears/develops and persist for more than 72 hours.

KEEP OUT OF REACH OF CHILDREN

Keep out of reach of childrenexcept under adult supervision.If swallowed, get medical help or contact a Poison Control Center right away.

Directions

- Slowly peel back label and use one wipe. Reseal, keep closed to prevent evaporation.
- Thoroughly wipe hands, allow to dry out rinsing.
- Discard after single use.

Inactive ingredients

Water, phenoxyethanol, ethylhexyl glycerin, didecyldimonium chloride, propylene glycol, glycerin, fragrance.